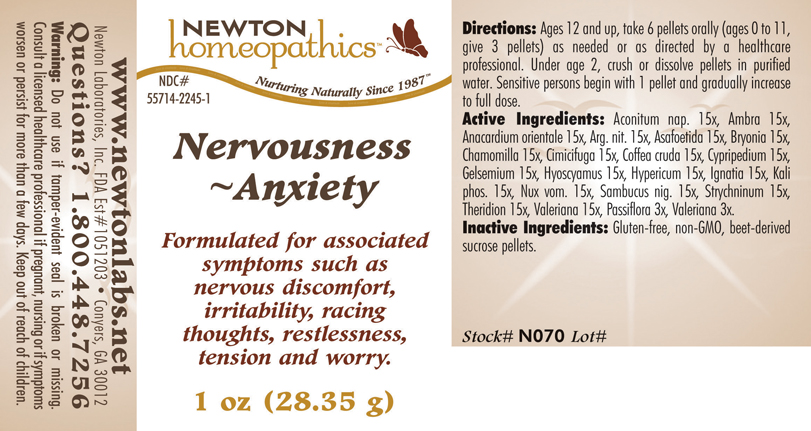 DRUG LABEL: Nervousness - Anxiety 
NDC: 55714-2245 | Form: PELLET
Manufacturer: Newton Laboratories, Inc.
Category: homeopathic | Type: HUMAN OTC DRUG LABEL
Date: 20110301

ACTIVE INGREDIENTS: Aconitum Napellus 15 [hp_X]/1 g; Ambergris 15 [hp_X]/1 g; Semecarpus Anacardium Juice 15 [hp_X]/1 g; Silver Nitrate 15 [hp_X]/1 g; Asafetida 15 [hp_X]/1 g; Bryonia Alba Root 15 [hp_X]/1 g; Matricaria Recutita 15 [hp_X]/1 g; Black Cohosh 15 [hp_X]/1 g; Arabica Coffee Bean 15 [hp_X]/1 g; Cypripedium Parvifolum Root 15 [hp_X]/1 g; Gelsemium Sempervirens Root 15 [hp_X]/1 g; Hyoscyamus Niger 15 [hp_X]/1 g; Hypericum Perforatum 15 [hp_X]/1 g; Strychnos Ignatii Seed 15 [hp_X]/1 g; Potassium Phosphate, Dibasic 15 [hp_X]/1 g; Strychnos Nux-vomica Seed 15 [hp_X]/1 g; Sambucus Nigra Flowering Top 15 [hp_X]/1 g; Strychnine 15 [hp_X]/1 g; Theridion Curassavicum 15 [hp_X]/1 g; Valerian 15 [hp_X]/1 g; Passiflora Incarnata Flowering Top 3 [hp_X]/1 g
INACTIVE INGREDIENTS: Sucrose

Nervousness - Anxiety

INDICATIONS & USAGE SECTION

Nervousness - Anxiety Formulated for associated symptoms such as nervous discomfort, irritability, racing thoughts, restlessness, tension and worry.

DOSAGE & ADMINISTRATION SECTION

Directions: Ages 12 and up, take 6 pellets orally (ages 0 to 11, give 3 pellets) as needed or as directed by a healthcare professional. Under age 2, crush or dissolve pellets in purified water. Sensitive persons begin with 1 pellet and gradually increase to full dose.

OTC - ACTIVE INGREDIENT SECTION

Aconitum nap. 15x, Ambra 15x, Anacardium orientale 15x, Arg. nit. 15x, Asafoetida 15x, Bryonia 15x, Chamomilla 15x, Cimicifuga 15x, Coffea cruda 15x, Cypripedium 15x, Gelsemium 15x, Hyoscyamus 15x, Hypericum 15x, Ignatia 15x, Kali phos. 15x, Nux vom. 15x, Sambucus nig. 15x, Strychninum 15x, Theridion 15x, Valeriana 15x, Passiflora 3x, Valeriana 3x.

OTC - PURPOSE SECTION

Formulated for associated symptoms such as nervous discomfort, irritability, racing thoughts, restlessness, tension and worry.

INACTIVE INGREDIENT SECTION

Inactive Ingredients: Gluten-free, non-GMO, beet-derived sucrose pellets.

QUESTIONS SECTION

www.newtonlabs.net Newton Laboratories, Inc. FDA Est # 1051203 - Conyers, GA 30012
Questions? 1.800.448.7256

WARNINGS SECTION

Warning: Do not use if tamper - evident seal is broken or missing. Consult a licensed healthcare professional if pregnant, nursing or if symptoms worsen or persist for more than a few days. Keep out of reach of children.

OTC - PREGNANCY OR BREAST FEEDING SECTION

Consult a licensed healthcare professional if pregnant, nursing or if symptoms worsen or persist for more than a few days.

OTC - KEEP OUT OF REACH OF CHILDREN SECTION

Keep out of reach of children.